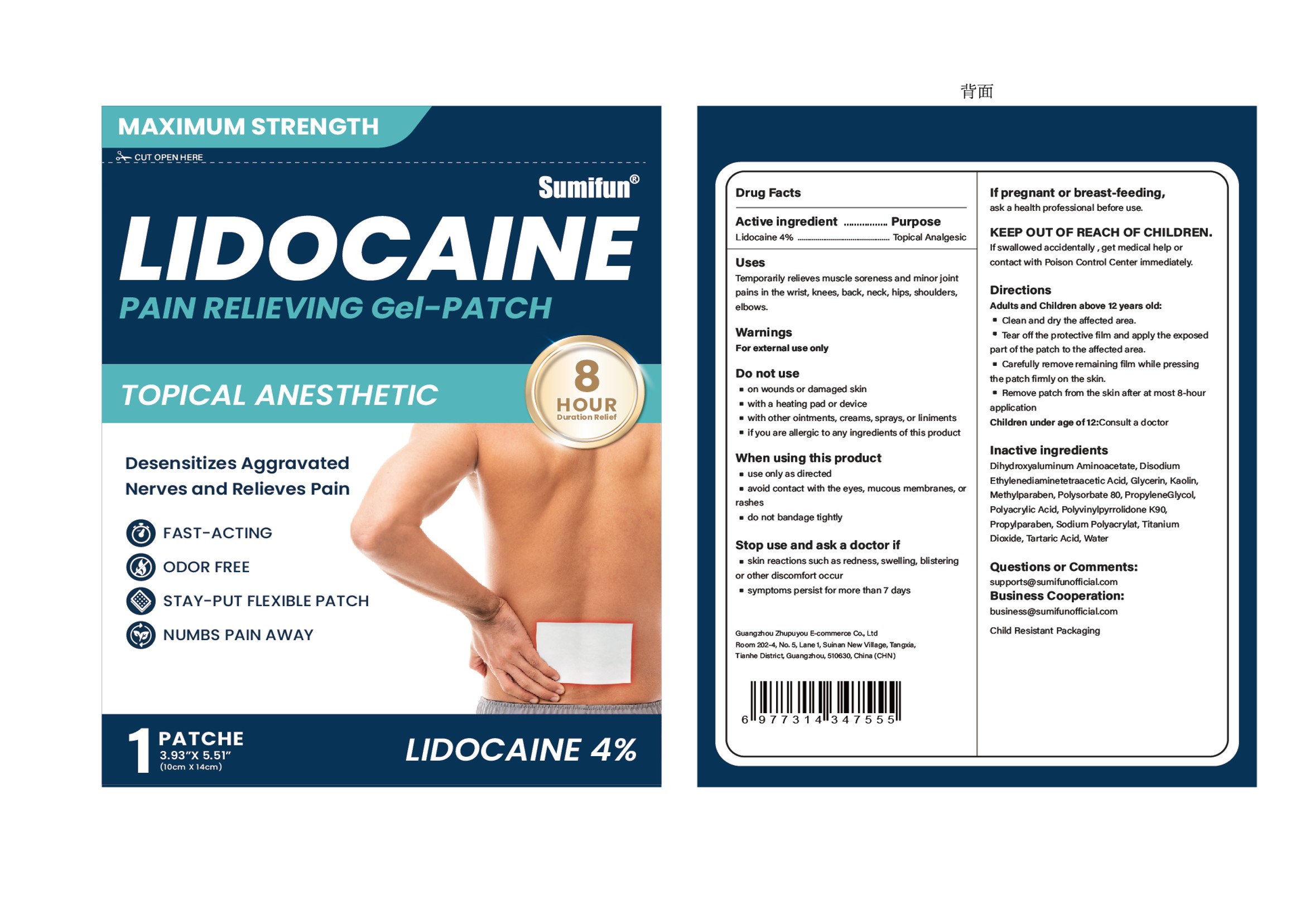 DRUG LABEL: LIDOCAINE PAIN RELIEVING Gel-Patch
NDC: 84165-103 | Form: PATCH
Manufacturer: Guangzhou Zhupuyou E-commerce Co., Ltd
Category: otc | Type: HUMAN OTC DRUG LABEL
Date: 20260108

ACTIVE INGREDIENTS: LIDOCAINE 0.04 g/1 g
INACTIVE INGREDIENTS: GLYCERIN; POLYSORBATE 80; POVIDONE K90; SODIUM POLYACRYLATE (2500000 MW); PROPYLENE GLYCOL; EDETATE DISODIUM; TARTARIC ACID; PROPYLPARABEN; WATER; DIHYDROXYALUMINUM AMINOACETATE ANHYDROUS; METHYLPARABEN; KAOLIN; TITANIUM DIOXIDE; POLYACRYLIC ACID (250000 MW)

84165-103 LIDOCAINE PAIN RELIEVING GEL-PATCH

LIDOCAINE PAIN RELIEVING GEL-PATCH

ACTIVE INGREDIENT

LIDOCAINE 4%

PURPOSE

Topical Analgesic

INDICATIONS AND USAGE

Temporarly relieves muscle soreness and minor jointpains in the wrist, knees, back, neck, hips, shoulders,elbows.

WARNINGS

For external use only

DO NOT USE

on wounds or damaged skin
with a heating pad or device
with other ointments, creams, sprays, or liniments
if you are allergic to any ingredients of this product

WHEN USING

use only as directed
avoid contact with the eyes, mucous membranes, or rashes
do not bandage tightly

STOP USE

skin reactions such as redness, swelling, blistering or other discomfort occur
symptoms persist for more than 7 days

KEEP OUT OF REACH OF CHILDREN

Ifswallowed accidentally , get medical help orcontact with Poison Control Center immediately.

DOSAGE AND ADMINISTRATION

Adults and Children above 12 years old:
Clean and dry the affected area.
Tear off the protective film and apply the exposedpart of the patch to the affected area.
Carefully remove remaining film while pressingthe patch fimly on the skin.
Remove patch from the skin after at most 8-hourapplication
Children under age of 12:Consult a doctor

INACTIVE INGREDIENT

Dihydroxyaluminum Aminoacetate Anhydrous
Edetate Disodium
Glycerin
Kaolin
Methylparaben
Polyacrylic Acid
Polysorbate 80
PolyvinylPyrrolidone K90
Propylene Glycol
Propylparaben
Sodium Polyacrylate
Tartaric Acid
Titanium Dioxide
Water